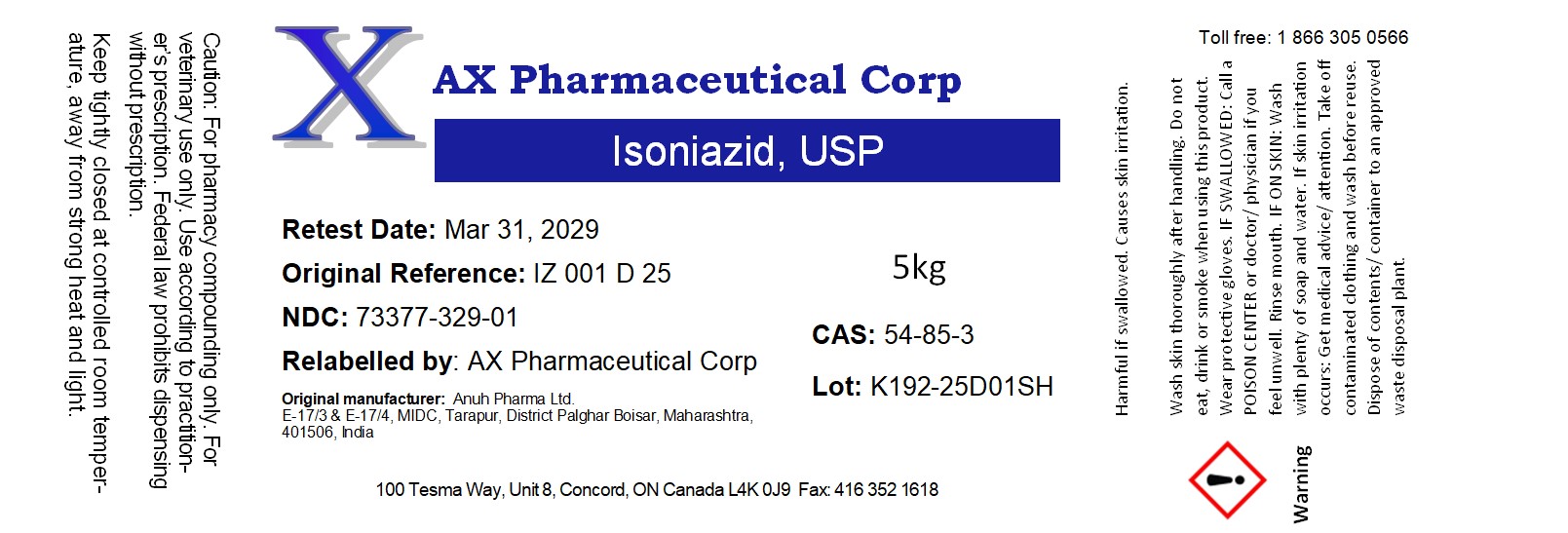 DRUG LABEL: Isoniazid
NDC: 73377-329 | Form: POWDER
Manufacturer: AX Pharmaceutical Corp
Category: other | Type: BULK INGREDIENT - ANIMAL DRUG
Date: 20250808

ACTIVE INGREDIENTS: ISONIAZID 1 g/1 g

Isoniazid